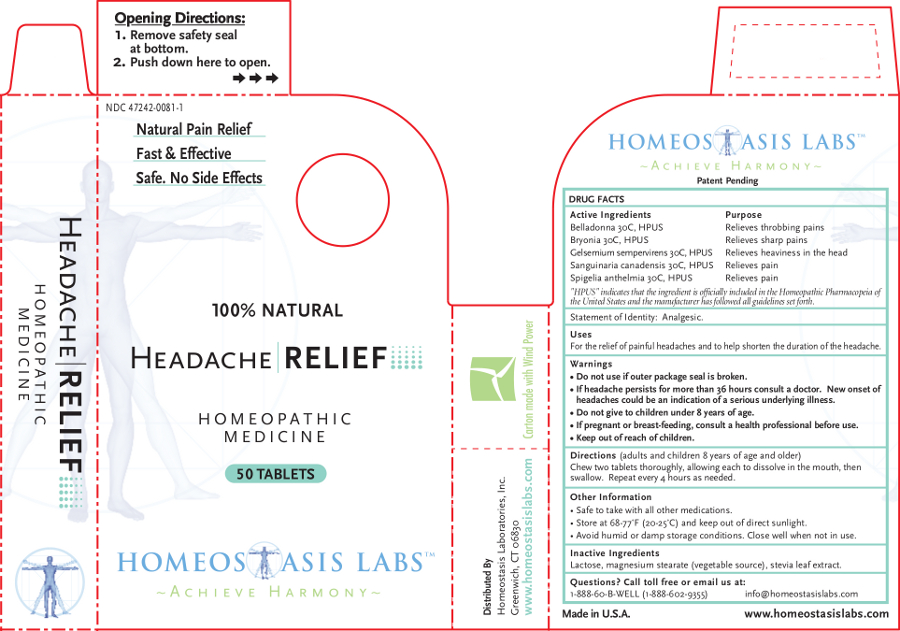 DRUG LABEL: Headache RELIEF
NDC: 47242-0081 | Form: TABLET, CHEWABLE
Manufacturer: Homeostasis Laboratories, Inc.
Category: homeopathic | Type: HUMAN OTC DRUG LABEL
Date: 20121114

ACTIVE INGREDIENTS: BRYONIA ALBA ROOT 30 [hp_C]/1 1; GELSEMIUM SEMPERVIRENS ROOT 30 [hp_C]/1 1; SANGUINARIA CANADENSIS ROOT 30 [hp_C]/1 1; SPIGELIA ANTHELMIA 30 [hp_C]/1 1
INACTIVE INGREDIENTS: LACTOSE; MAGNESIUM STEARATE; STEVIA REBAUDIUNA LEAF

Headache RELIEF

Active Ingredients | Purpose
Belladonna 30C, HPUS | Relieves throbbing pains
Bryonia 30C, HPUS | Relieves sharp pains
Gelsemium sempervirens 30C, HPUS | Relieves heaviness in the head
Sanguinaria canadensis 30C, HPUS | Relieves pain
Spigelia anthelmia 30C, HPUS | Relieves pain

"HPUS" indicates that the ingredient is officially included in the Homeopathic Pharmacopeia of the United States and the manufacturer has followed all guidelines set forth.

Statement of Identity: Analgesic.

Uses

For the relief of painful headaches and to help shorten the duration of the headache.

Warnings

- Do not use if outer package seal is broken.
- If headache persists for more than 36 hours consult a doctor. New onset of headaches could be an indication of a serious underlying illness.
- Do not give to children under 8 years of age.

PREGNANCY OR BREAST FEEDING

- If pregnant or breast-feeding, consult a health professional before use.

- Keep out of reach of children.

Directions

(adults and children 8 years of age and older)

Chew two tablets thoroughly, allowing each to dissolve in the mouth, then swallow. Repeat every 4 hours as needed.

Other information

- Safe to take with all other medications.
- Store at 68-77°F (20-25°C) and keep out of direct sunlight.
- Avoid humid or damp storage conditions. Close well when not in use.

Inactive Ingredients

Lactose, magnesium stearate (vegetable source), stevia leaf extract.

Questions? Call toll free or email us at:

1-888-60-B-WELL (1-888-602-9355)

info@homeostasislabs.com